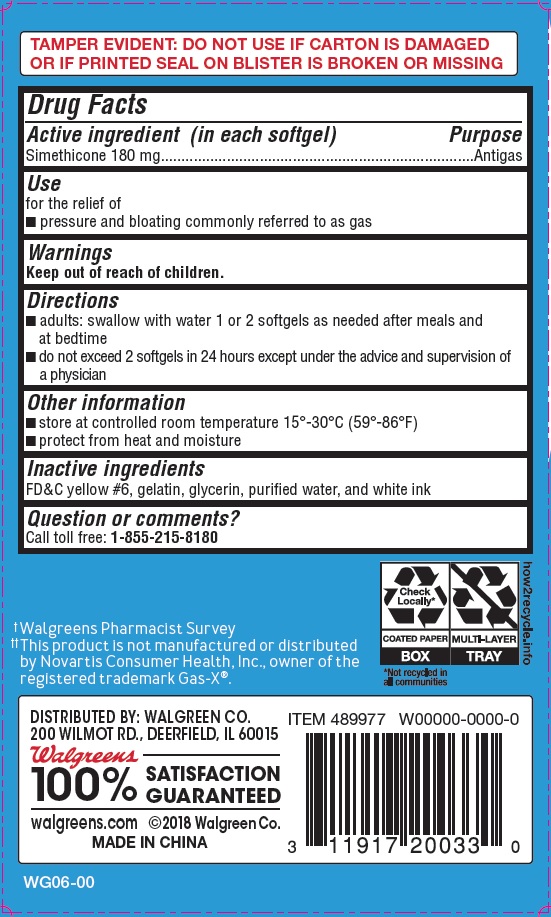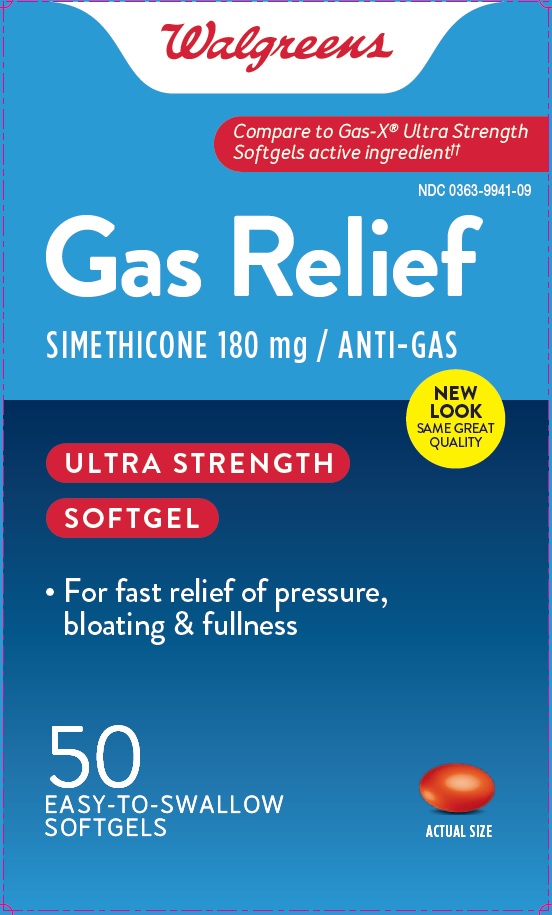 DRUG LABEL: Ultra Strength Gas Relief
NDC: 0363-9941 | Form: CAPSULE, LIQUID FILLED
Manufacturer: Walgreen Co.
Category: otc | Type: HUMAN OTC DRUG LABEL
Date: 20241121

ACTIVE INGREDIENTS: DIMETHICONE 180 mg/1 1
INACTIVE INGREDIENTS: FD&C YELLOW NO. 6; GELATIN; GLYCERIN; WATER

Ultra Strength Gas Relief

Drug Facts

Active ingredient (in each softgel)

Simethicone 180 mg

Purpose

Antigas

Uses

for the relief of

- pressure and bloating commonly referred to as gas

Warnings

Keep out of reach of children.

Directions

- adults: swallow with water 1 or 2 softgels as needed after meals and at bedtime
- do not exceed 2 softgels in 24 hours except under the advice and supervision of a physician

Other information

- store at controlled room temperature 15º - 30ºC (59º - 86ºF)
- protect from heat and moisture

Inactive ingredients

FD&C yellow#6, gelatin, glycerin, purified water and white ink

Questions or comments?

Call: 1-855-215-8180

PRINCIPAL DISPLAY PANEL

Ultra Strength Gas Relief

Simethicone 180 mg Antigas 50 Softgels

NDC 0363-9941-09

*Compare to the active ingredient in Gas-X®Ultra Strength